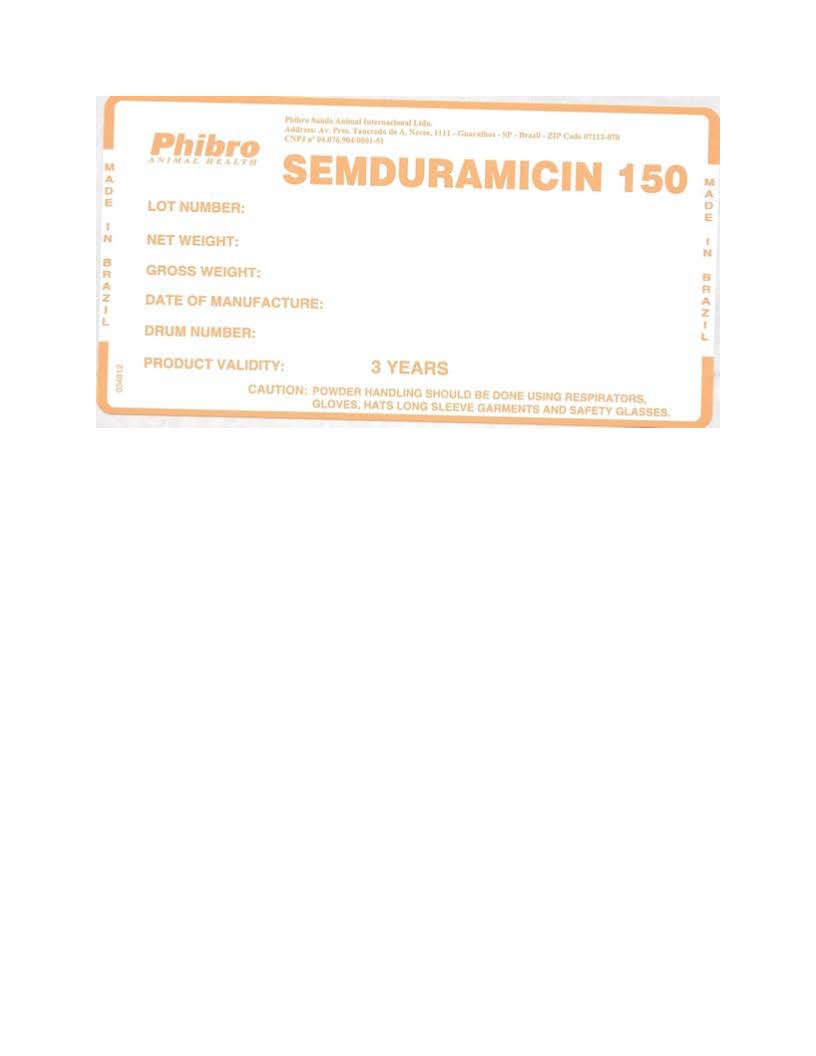 DRUG LABEL: SEMDURAMICIN 150
NDC: 44476-0676 | Form: POWDER
Manufacturer: Phibro Saude Animal Internacional Ltda
Category: other | Type: BULK INGREDIENT - ANIMAL DRUG
Date: 20220628

ACTIVE INGREDIENTS: SEMDURAMICIN 100 kg/100 kg

SEMDURAMICIN

Generic Section

LOT NUMBER:

NET WEIGHT:

GROSS WEIGHT:

DATE OF MANUFACTURE:

DRUM NUMBER:

RETEST DATE: 3 YEARS

Caution:

For Manufacturing, Processing or Repacking use only.

Caution:

Powder handling should be done using respirators, gloves, hats, long sleeve garments and safety glasses.

Manufactured By:

Phibro Saúde Animal Internacional Ltda.

Av. Pres. Tancredo de Almeida Neves 1.063

Guarulhos, São Paulo 07112, Brazil

CNPJ n° 04.076.904/0001-51

PACKAGE LABEL

Add image transcription here...